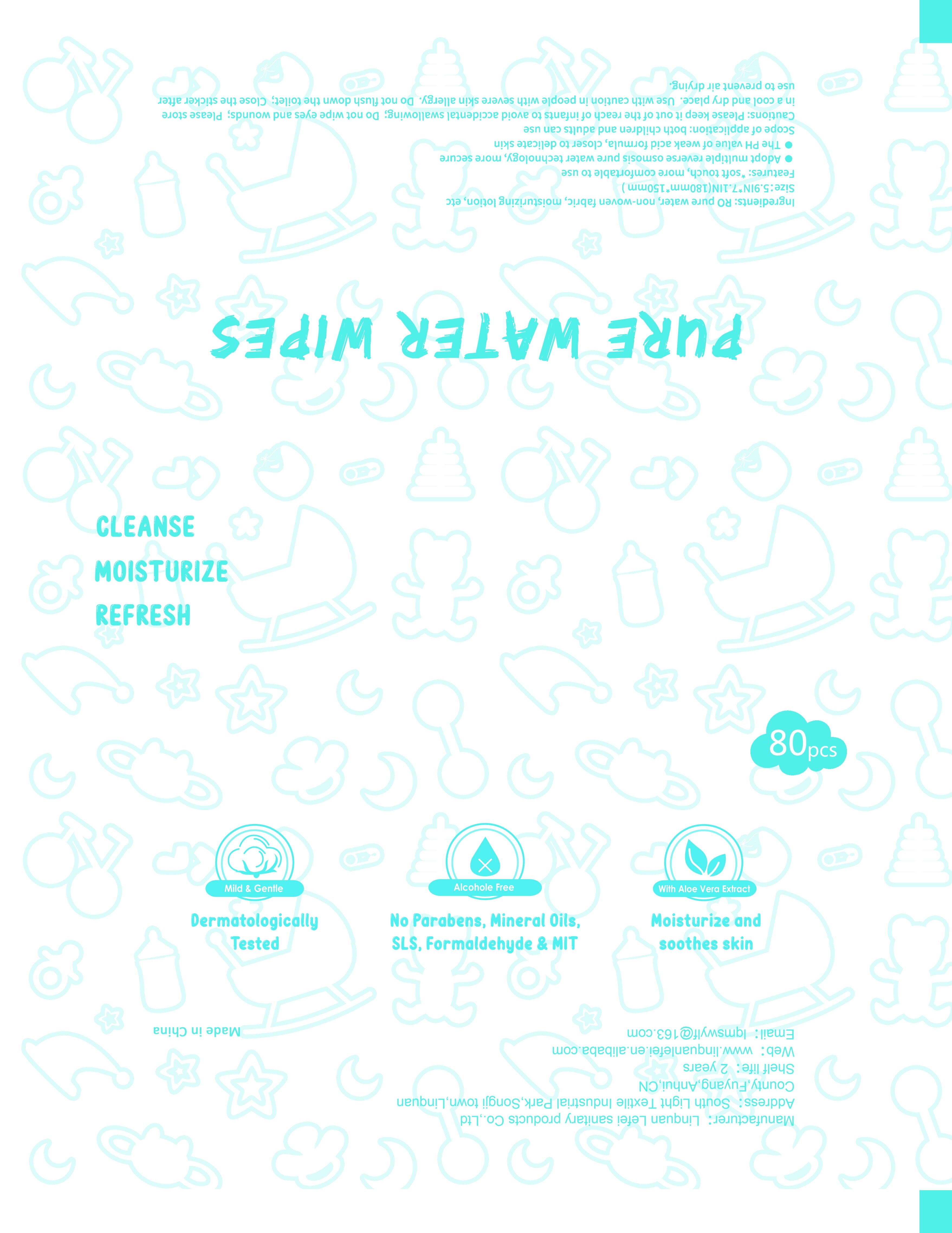 DRUG LABEL: Disinfecting wipe
NDC: 83130-101 | Form: CLOTH
Manufacturer: Linquan Lefei sanitary products Co.,Ltd
Category: otc | Type: HUMAN OTC DRUG LABEL
Date: 20240523

ACTIVE INGREDIENTS: ALCOHOL 1 mL/1 mL
INACTIVE INGREDIENTS: BENZETHONIUM CHLORIDE; WATER

Disinfecting wipe

Disinfecting wipe

Active Ingredient

75%ALCOHOL .Bacteriostasis, Sterilization

Purpose

Soft nonwoven fabrics contain special essential ingredients. Alcoro is free, mixed with purewater. Effective cleaning. You feel comfortable with fresh cleaning wipes.

Use

Bacteriostasis, Sterilization

pull the protective seal back in the direction shown and pull out the wipes as required.Close the seal after each use and keep the wipes moist.

Do not expose to direct sunlight orHigh temperature, for externaluse only.

Warnings

1.Keep away from the baby.
2.Avoid contact with eyes orwounds.
3. Don't flush the wipes into the toilet.
4.Do not expose to direct sunlight orHigh temperature, for externaluse only.

DO NOT USE

1.Keep away from the baby.
2.Avoid contact with eyes orwounds.
3. Don't flush the wipes into the toilet.
4.Do not expose to direct sunlight orHigh temperature, for externaluse only.

WHEN USING

1.Keep away from the baby.
2.Avoid contact with eyes orwounds.
3.Don't flush the wipes into the toilet.
4.Do not expose to direct sunlight orHigh temperature, for externaluse only.

Keep away from the baby.

DOSAGE AND ADMINISTRATION

Pull the protective seal back in the direction shown and pull out the wipes as required.close the seal after each use and keep the wipes moist.

STORAGE AND HANDLING

Do not expose to direct sunlight orHigh temperature.
Close the seal after each use and keep the wipes moist.

INACTIVE INGREDIENT

Water,BENZETHONIUM CHLORIDE